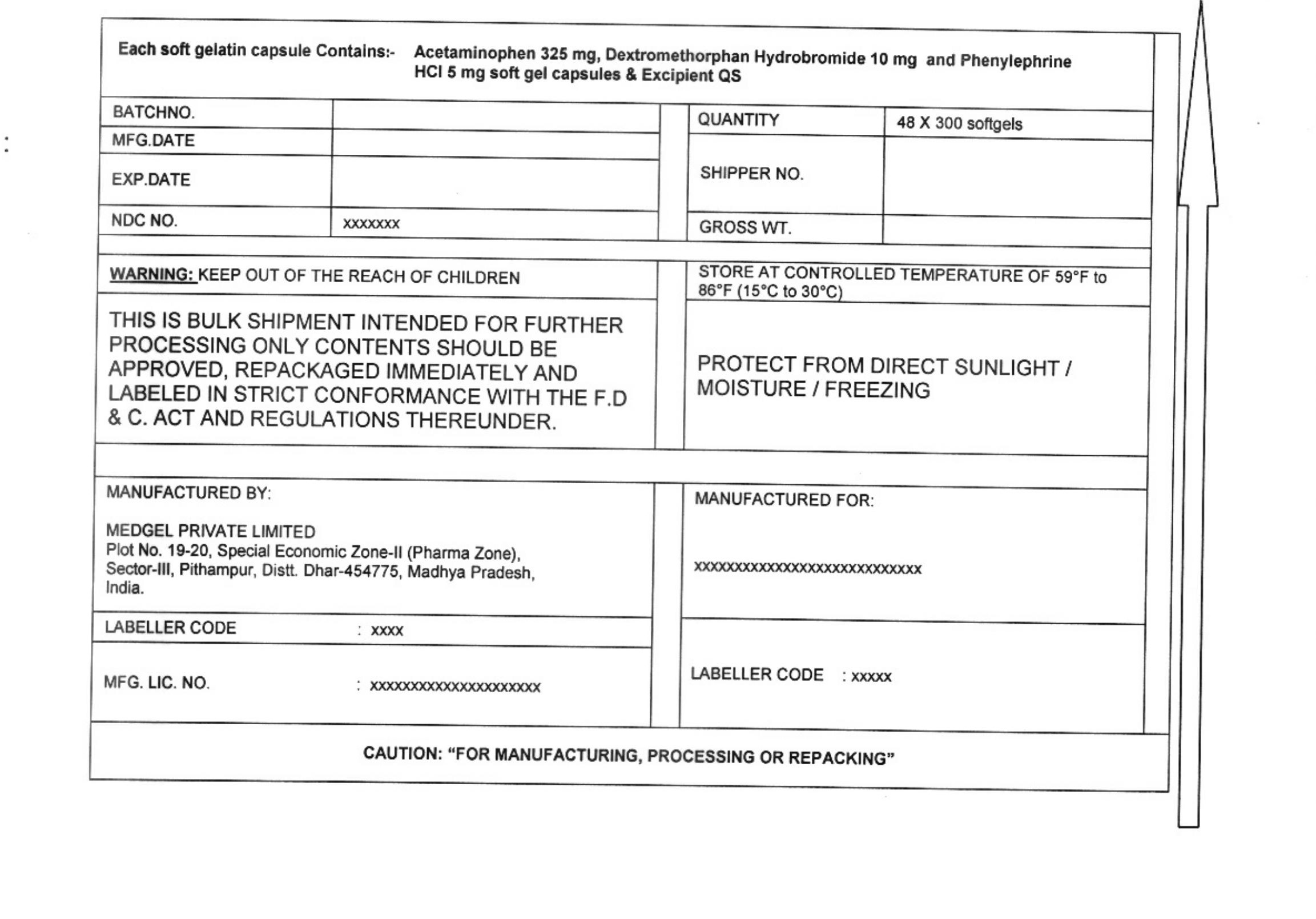 DRUG LABEL: acetaminophen, dextromethorphan hydrobromide, phenylephrine hydrochloride
NDC: 55629-012 | Form: CAPSULE, LIQUID FILLED
Manufacturer: ONE2ZEE LIMITED LIABILITY COMPANY
Category: otc | Type: HUMAN OTC DRUG LABEL
Date: 20230325

ACTIVE INGREDIENTS: ACETAMINOPHEN 325 mg/1 1; DEXTROMETHORPHAN HYDROBROMIDE 10 mg/1 1; PHENYLEPHRINE HYDROCHLORIDE 5 mg/1 1
INACTIVE INGREDIENTS: POLYETHYLENE GLYCOL 400; PROPYLENE GLYCOL; POVIDONE K30; FD&C RED NO. 40; FD&C YELLOW NO. 6; TITANIUM DIOXIDE; GELATIN; GLYCERIN; SORBITOL; WATER

DayTime Cold and Flu capsule, liquid filled (Acetaminophen 325mg, Dextromethorphan HBr 10mg, Phenylephrine HCl 5mg)

Active ingredients (in each capsule)

Acetaminophen 325 mg

Dextromethorphan HBr 10 mg

Phenylephrine HCl 5 mg

Purose

- Pain reliever/ fever reducer
- Cough suppressant
- Nasal decongestant

Uses

temporarily relieves common cold/flu symptoms:

- cough due to minor throat & bronchial irritation
- nasal congestion
- sore throat
- headache
- minor aches/pains
- fever

WARNINGS

Alcohol warning: If you consume 3 or more alcoholic drinks every day, ask your doctor whether you should take acetaminophen or other pain relievers/fever reducers. Acetaminophen may cause liver damage.

Sore throat warning: If sore throat is severe, persists for more than two days, is accompanied or followed by fever, headache, rash, nausea, or vomiting, consult a doctor promptly.

Do Not Use

- with other medicines containing acetaminophen
- if you are now taking a prescription monoamine oxidase inhibitor (MAOI) (certain drugs for depression, psychiatric or emotional conditions, or Parkinson's disease), or for 2 weeks after stopping the MAOI drug. If you do not know if your prescription drug contains an MAOI, ask a doctor or pharmacist before taking this product.

Ask a doctor before use if you have

- heart disease
- thyroid disease
- diabetes
- high blood pressure
- trouble urinating due to enlarged prostate gland
- cough that occurs with too much phlegm (mucus)
- persistent or chronic cough as occurs with smoking, asthma, or emphysema

Stop use and ask a doctor if

- you get nervous, dizzy or sleepless
- symptoms get worse or last more than 5 days (children) or 7 days (adults)
- fever gets worse or lasts more than 3 days
- redness or swelling is present
- new symptoms occur
- cough comes back, or occurs with rash or headache that lasts.

These could be signs of a serious condition.

Directions

- take only as recommended - see OVERDOSE warning
- do not exceed 6 doses per 24 hours

Adults and children 12 years of age and older | 2 LiquiCaps with water every 4 hours
Children under 12 years of age | ask doctor

When using other DayQuil or NyQuil products, carefully read each label to insure correct dosing

Other Information

- store at room temperature 59°-86°F (15°-30°C)

Inactive ingredients

polyethylene glycol 400, propylene glycol, povidone k30, fd&c red no. 40, fd&c yellow no. 6, titanium dioxide, gelatin, glycerin, sorbitol, water

PRINCIPAL DISPLAY PANEL - Shipping Label

Acetaminophen, Dextromethorphan HBr Phenylephrine HCL capsules

Each Softgel Contains:
(Acetaminophen USP 325 mg, Dextromethorphan Hydrobromide USP 10 mg,
Phenylephrine Hydrochloride USP 5mg)

LOT NO:
DRUM NO:
MFG DATE:
QUANTITY:
NDC NO: 55629-012-
EXP DATE:

WARNING:
KEEP OUT OF REACH OF CHILDREN

STORE CONTROLLED ROOM TEMPERATURE OF 59° - 86°F (15° - 30°C)
PROTECT FROM LIGHT, MOISTURE AND FREEZING

THIS IS A BULK SHIPMENT INTENDED FOR FURTHER PROCESSING ONLY.

CONTENTS SHOULD BE APPROVED, REPACKAGED IMMEDIATELY AND LABELED IN STRICT CONFORMANCE WITH
THE F.D & C.ACT AND REGULATIONS THEREUNDER.